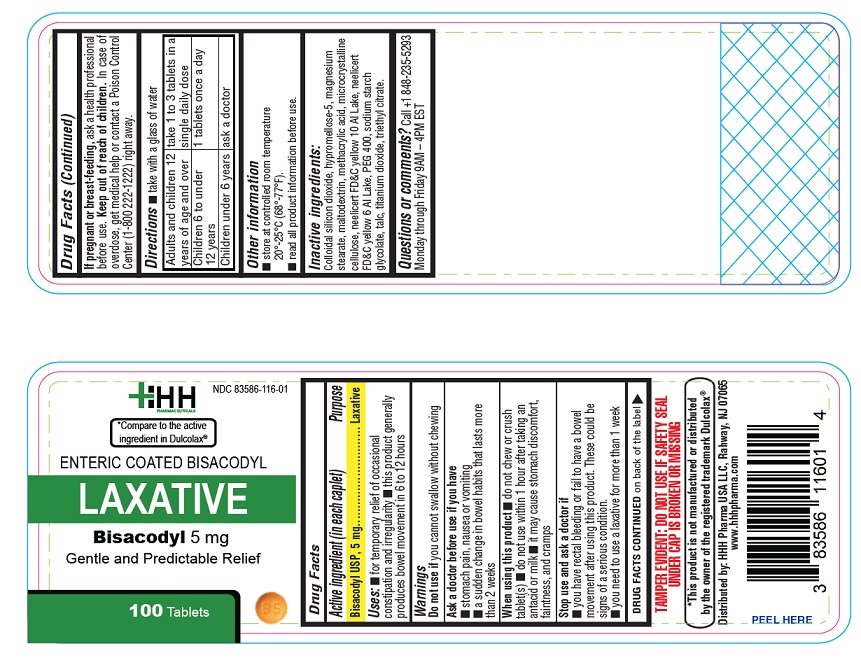 DRUG LABEL: Laxative
NDC: 83586-116 | Form: TABLET, DELAYED RELEASE
Manufacturer: HHH PHARMA USA LLC
Category: otc | Type: HUMAN OTC DRUG LABEL
Date: 20250728

ACTIVE INGREDIENTS: BISACODYL 5 mg/1 1
INACTIVE INGREDIENTS: SILICON DIOXIDE; HYPROMELLOSE 2910 (5 MPA.S); MAGNESIUM STEARATE; MALTODEXTRIN; METHACRYLIC ACID; MICROCRYSTALLINE CELLULOSE; D&C YELLOW NO. 10 ALUMINUM LAKE; FD&C YELLOW NO. 6 ALUMINUM LAKE; POLYETHYLENE GLYCOL 400; SODIUM STARCH GLYCOLATE TYPE A; TALC; TITANIUM DIOXIDE; TRIETHYL CITRATE

Active ingredient (in each tablet)

Bisacodyl USP, 5 mg

Purpose

Laxative

Uses

- for temporary relief of occasional constipation and irregularity
- this product generally produces bowel movement in 6 to 12 hours

Warnings

Do not use

if you cannot swallow without chewing

Ask a doctor before use if you have

- stomach pain, nausea or vomiting
- a sudden change in bowel habits that lasts more than 2 weeks

When using this product

- do not chew or crush tablet(s)
- do not use within 1 hour after taking an antacid or milk
- it may cause stomach discomfort, faintness, and cramps

Stop use and ask a doctor if

- you have rectal bleeding or fail to have a bowel movement after using this product. These could be signs of a serious condition.
- you need to use a laxative for more than 1 week

If pregnant or breast-feeding,

ask a health professional before use.

Keep out of reach of children.

In case of overdose, get medical help or contact a Poison Control Center (1-800-222-1222) right away.

Directions

- take with a glass of water

adults and children 12 years of age and over | take 1 to 3 tablets in a single daily dose
children 6 to under 12 years | 1 tablets once a day
children under 6 years | ask a doctor

Other information

- store at controlled room temperature 20°-25°C (68°-77°F)
- read all product information before use.

Inactive ingredients

Colloidal silicon dioxide, hypromellose-5, magnesium stearate, maltodextrin, methacrylic acid, microcrystalline cellulose, neelicert FD&C yellow 10 Al Lake, neelicert FD&C yellow 6 Al Lake, PEG 400, sodium starch glycolate, talc, titanium dioxide, triethyl citrate.

Questions or comments?

Call + 1-848-235-5293

Monday through Friday 9AM – 5PM EST